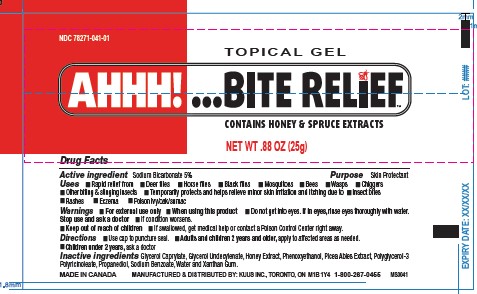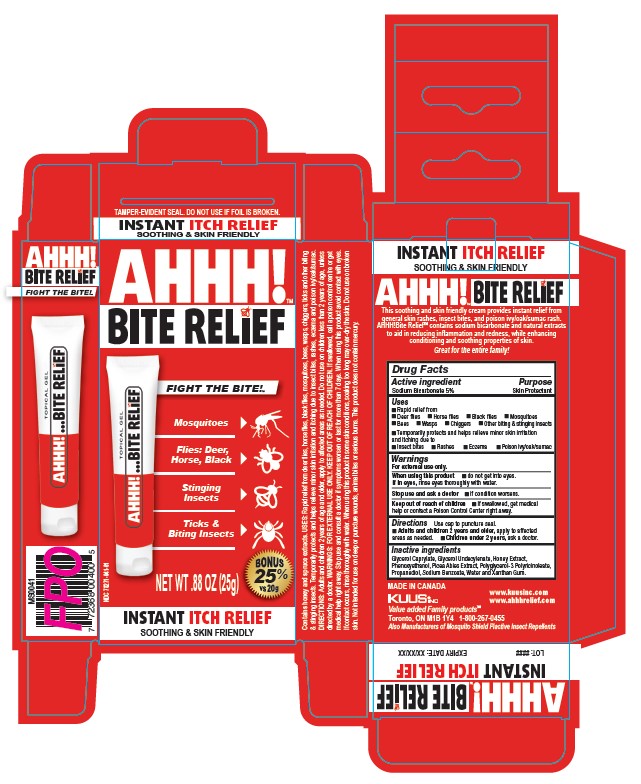 DRUG LABEL: AHHH Bite Relief
NDC: 78271-041 | Form: GEL
Manufacturer: 78271
Category: otc | Type: HUMAN OTC DRUG LABEL
Date: 20250527

ACTIVE INGREDIENTS: SODIUM BICARBONATE 5 g/25 g
INACTIVE INGREDIENTS: SODIUM BENZOATE; GLYCERYL CAPRYLATE; PHENOXYETHANOL; PICEA ABIES LEAF OIL; PROPANEDIOL; XANTHAN GUM; WATER; GLYCERYL MONOUNDECYLENATE; HONEY; POLYGLYCERYL-3 RICINOLEATE

Active Ingredient

Sodium Bicarbonate 5%

Purpose

Skin Protectant

Uses

Rapid relief from

- Deer flies
- Horse flies
- Black flies
- Mosquitoes
- Bees
- Wasps
- Chiggers
- Other biting & stinging insects

Temporarily protects and helps relieve minor skin irritation and itching due to

- Insect bites
- Rashes
- Eczema
- Poison ivy/oak/sumac

WARNINGS

For external use only.

When using this product

- do not get into eyes. If in eyes, rinse thoroughly wiht water.

Stop use and ask a doctor

- if condition worsens.

Keep out of reach of children

- If swallowed, get medical help or contact a Poison control Center right away.

Directions

Use cap to puncture seal.

- Adults and children 2 years and older, apply to affedtec areas as needed.
- Children under 2 years, ask a doctor.

INACTIVE INGREDIENT

Glycerol Caprylate, Glycerol Undecylenate, Honey Extract, Phenoxyethanol, Picea Abies Extract, Polyglycerol-3 Polyricinoleate, Propanediol, Sodium Benzoate, Water and Xanthan Gum.